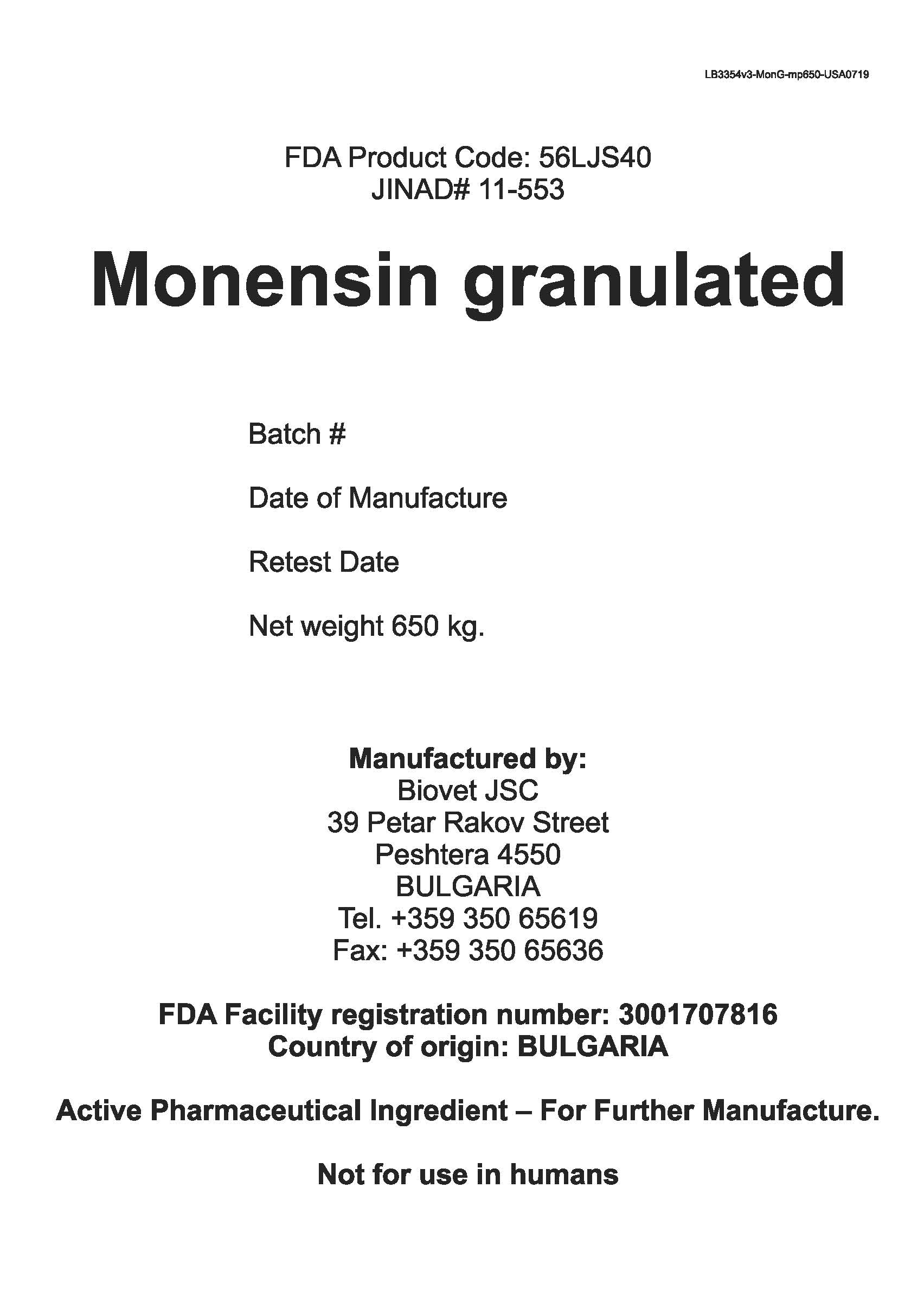 DRUG LABEL: Monensin Granulated
NDC: 11311-971 | Form: powder
Manufacturer: Biovet Joint Stock Company
Category: other | Type: BULK INGREDIENT - ANIMAL DRUG
Date: 20200305

ACTIVE INGREDIENTS: MONENSIN 1 kg/1 kg

Monensin Granulated